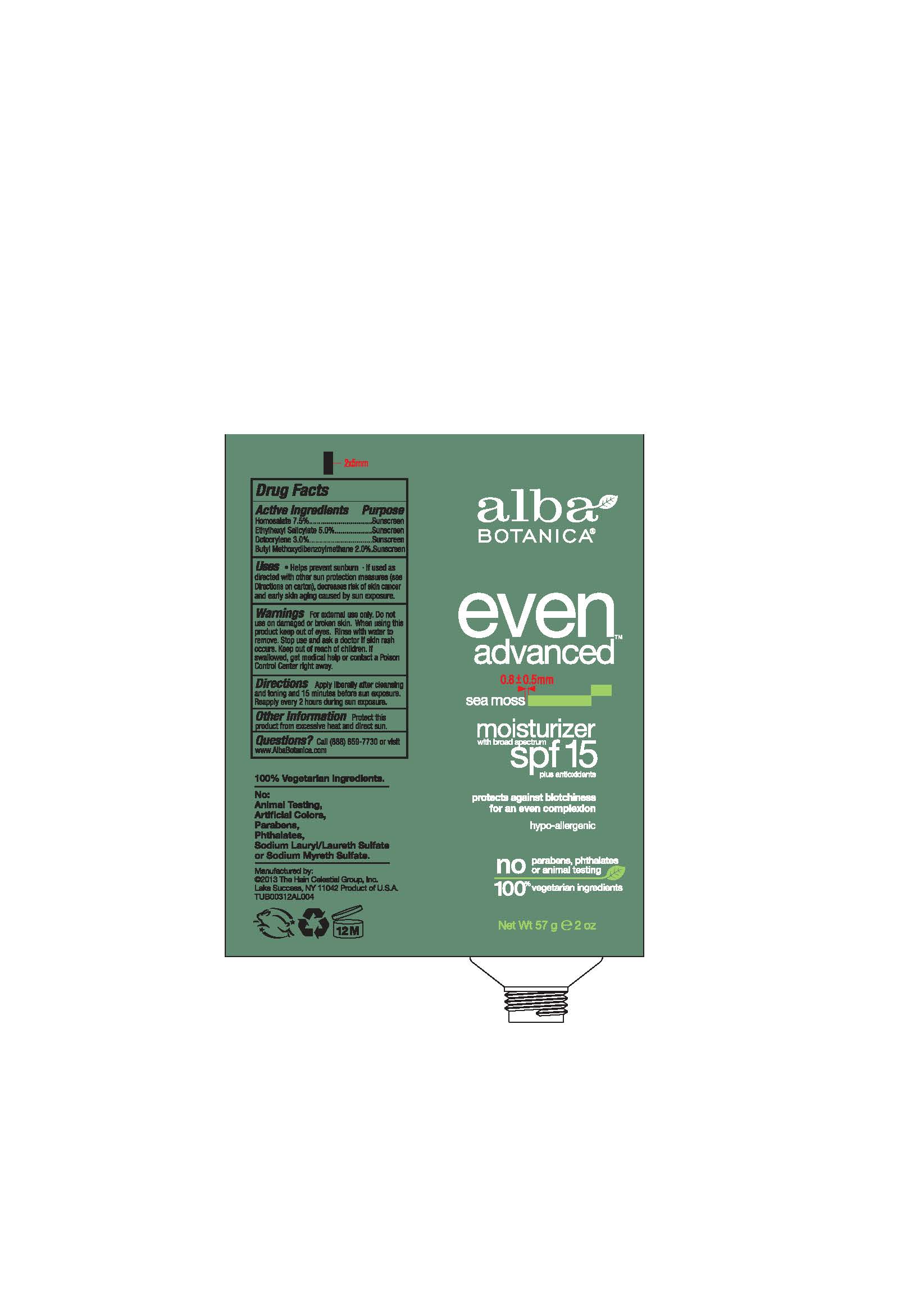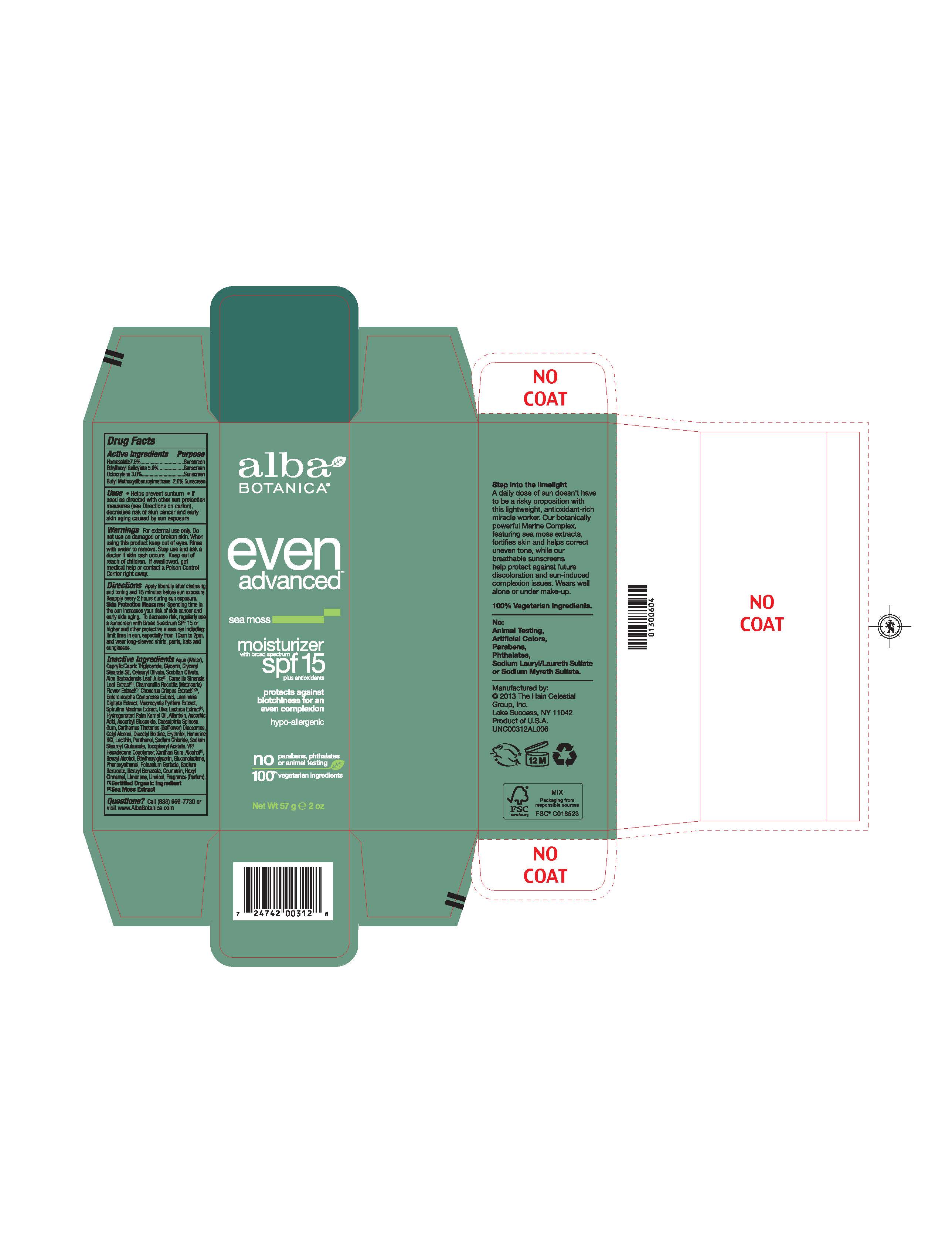 DRUG LABEL: Alba Even Advanced Sea Moss Moisturizer SPF15
NDC: 61995-2031 | Form: LOTION
Manufacturer: The Hain Celestial Group, Inc.
Category: otc | Type: HUMAN OTC DRUG LABEL
Date: 20221202

ACTIVE INGREDIENTS: HOMOSALATE 7.5 g/100 g; OCTISALATE 5 g/100 g; OCTOCRYLENE 3 g/100 g; AVOBENZONE 2 g/100 g
INACTIVE INGREDIENTS: ETHYLHEXYLGLYCERIN; ALCOHOL; ULVA LACTUCA; BENZYL ALCOHOL; PHENOXYETHANOL; ALOE VERA LEAF; GLYCERIN; WATER; VINYLPYRROLIDONE/HEXADECENE COPOLYMER; SODIUM STEAROYL GLUTAMATE; .ALPHA.-TOCOPHEROL ACETATE; GLYCERYL STEARATE SE; POTASSIUM SORBATE; CETYL ALCOHOL; ASCORBYL GLUCOSIDE; GREEN TEA LEAF; CHAMOMILE; XANTHAN GUM; HYDROGENATED PALM KERNEL OIL; LECITHIN, SOYBEAN; MEDIUM-CHAIN TRIGLYCERIDES; CAESALPINIA SPINOSA RESIN; CETEARYL OLIVATE; SODIUM CHLORIDE; SORBITAN OLIVATE; SODIUM BENZOATE; HOMARINE HYDROCHLORIDE; CHONDRUS CRISPUS CARRAGEENAN; ULVA COMPRESSA; LAMINARIA DIGITATA; MACROCYSTIS PYRIFERA; SPIRULINA MAXIMA; ALLANTOIN; ASCORBIC ACID; CARTHAMUS TINCTORIUS SEED OLEOSOMES; DIACETYL BOLDINE; ERYTHRITOL; PANTHENOL; GLUCONOLACTONE

Active Ingredient

Homosalate - 7.5%

Octocrylene -3.0%

Ethylhexyl Salicylate - 5.0%

Butyl Methoxydibenzoylmethane - 2.0%

DOSAGE AND ADMINISTRATION

Apply liberally after cleansing and toning and 15 minutes before sun exposure. Reapply every 2 hours during sun exposure.

PURPOSE

Sunscreen

WARNINGS

For external use only. Do not use on damaged or broken skin. When using this product keep out of eyes. Rinse with water to remove. Stop use and ask a doctor if skin rash occurs.

Keep out of reach of children. If swallowed get medical help or contact Poison Center right away.

INACTIVE INGREDIENT

Water, Glycerin, Glyceryl Stearate SE, Cetyl Alcohol, VP/Hexadecene Copolymer, Caprylic/Capric Triglyceride, Hydrogenated Palm Cernel Oil, Aloe Barbadensis Leaf Juice(1), Camellia Sinensis Leaf Extract (1), Chamomilla Recutita (Matricaria) Flower Extract (1), Chondrus Crispus Extract (1), (2), Enteromorpha Compressa Extract, Laminaria Digitata Extract, Macrocystis Pyrifera Extract, Spirulina Maxima Extract, Ulva Lactuca Extract (1), Allantoin, Ascorbic Acid, Ascorbyl Glucoside, Caesalpinia Spinosa Gum, Carthamus Tinctorius (Safflower) Oleosomes, Cetearyl Olivate, , Lecithin, Diacetyl Boldine, Erythritol, Homarine HCL, Panthenol, Gluconolactone, Sodium Chloride, Sodium Stearoyl Glutamate, Sorbitan Olivate, Tocopheryl Acetat, Xanthan Gum, Alcohol (1), Benzyl Alcohol, Ethylhexylglycerin, Phenoxyethanol, Potassium Sorbate, Sodium Benzoate.

(1) Certified Organicf Ingredient, (2) Sea Moss Extract

INDICATIONS AND USAGE

Helps prevents sunburns. If used as directed with other sun protection measures, decreases risk of skin cancer and early skin aging caused by sun exposure. Skin Protection Measures: Spending time in the sun increases your risk of skin cancer and early skin aging. To decrease risk, regularly use sunscreen with Broad Spectrum SPF 15 or higher and other protective measures including: limit time in sun, especially from10am to 2pm, and wear long sleeved shirts, pants, hats and sunglases.